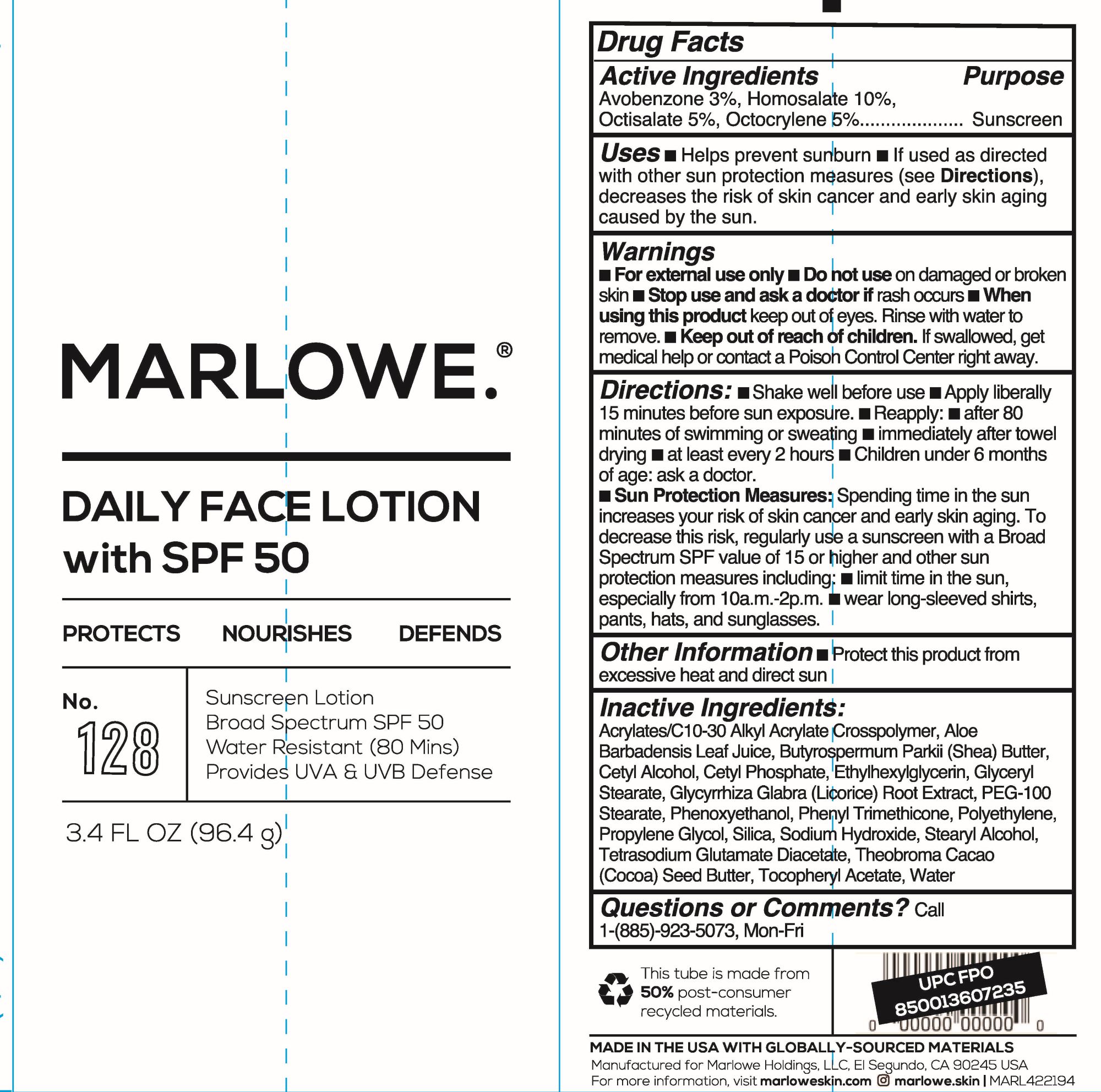 DRUG LABEL: Marlowe
NDC: 82215-0001 | Form: LOTION
Manufacturer: Marlowe Holdings, LLC
Category: otc | Type: HUMAN OTC DRUG LABEL
Date: 20241023

ACTIVE INGREDIENTS: OCTOCRYLENE 49.9 mg/1 mL; AVOBENZONE 29.94 mg/1 mL; OCTISALATE 49.9 mg/1 mL; HOMOSALATE 99.8 mg/1 mL
INACTIVE INGREDIENTS: ALPHA-TOCOPHEROL ACETATE; WATER; PEG-100 STEARATE; GLYCERYL MONOSTEARATE; PHENYL TRIMETHICONE; CARBOMER INTERPOLYMER TYPE A (55000 CPS); ALOE VERA LEAF; SHEA BUTTER; CETYL ALCOHOL; COCOA BUTTER; GLYCYRRHIZA GLABRA; PROPYLENE GLYCOL; SILICON DIOXIDE; STEARYL ALCOHOL; SODIUM HYDROXIDE; PHENOXYETHANOL; CETYL PHOSPHATE; HIGH DENSITY POLYETHYLENE; ETHYLHEXYLGLYCERIN; TETRASODIUM GLUTAMATE DIACETATE

Marlowe No. 128 Daily Face Lotion with SPF 50

Active Ingredient

Avobenzone 3%, Homosalate 10%, Octisalate 5%, Octocryle 5%

Purpose

Sunscreen

Uses

Helps prevent sunburn

If used as directed with other sun protection measures (see directions). Decreases the risk of skin cancer and early skin aging caused by the sun.

Warnings

For external use only

Do not use on

damaged or broken skin

When using this product

Keep out of eyes. Rinse wih water to remove.

Stop use and ask a doctor

If rash occurs

Keep out of reach of children

If swallowed, get medical help or contact a Poison Control Center right away.

Directions

Apply liberally 15 minutes before sun exposure.

Reapply: After 80 minutes of swimming and sweating.

Immediately after towel drying.

At least every 2 hours.

Sun Protection Measures. Spending time in the sun increases your risk of skin cancer and early skin aging. To decrease the risk, regularly use a sunscreen with a broad spectrum SPF value of 15 or higher and other sun protection measures including:

Limit time in the sun, especially from 10 a.m. to 2 p.m.

Wear long-sleeved shirts, pants, hats, and sunglasses. Children under 6 months: ask a doctor.

Inactive Ingredients

Acrylates/C10-30 Alkyl Acrylate Crosspolymer, Aloe Barbadensis Leaf Juice, Butyrospermum Parkii (Shea) Butter, Cetyl Alcohol, Cetyl Phosphate, Ethylhexylglycerin, Glyceryl Stearate, Glycyrrhiza Glabra (Licorice) Root Extract, PEG-100 Stearate, Phenoxyethanol, Phenyl Trimethicone, Polyethylene, Propylene Glycol, Silica, Sodium Hydroxide, Stearyl Alcohol, Tetrasodium Glutamate Diacetate, Theobroma Cacao (Cocoa) Seed Butter, Tocopheryl Acetate, Water

Ohter Information

Protect this product from excessive heat and direct sun.

Questions or Comments

Call 1-(855)-923-5073, Mon-Fri